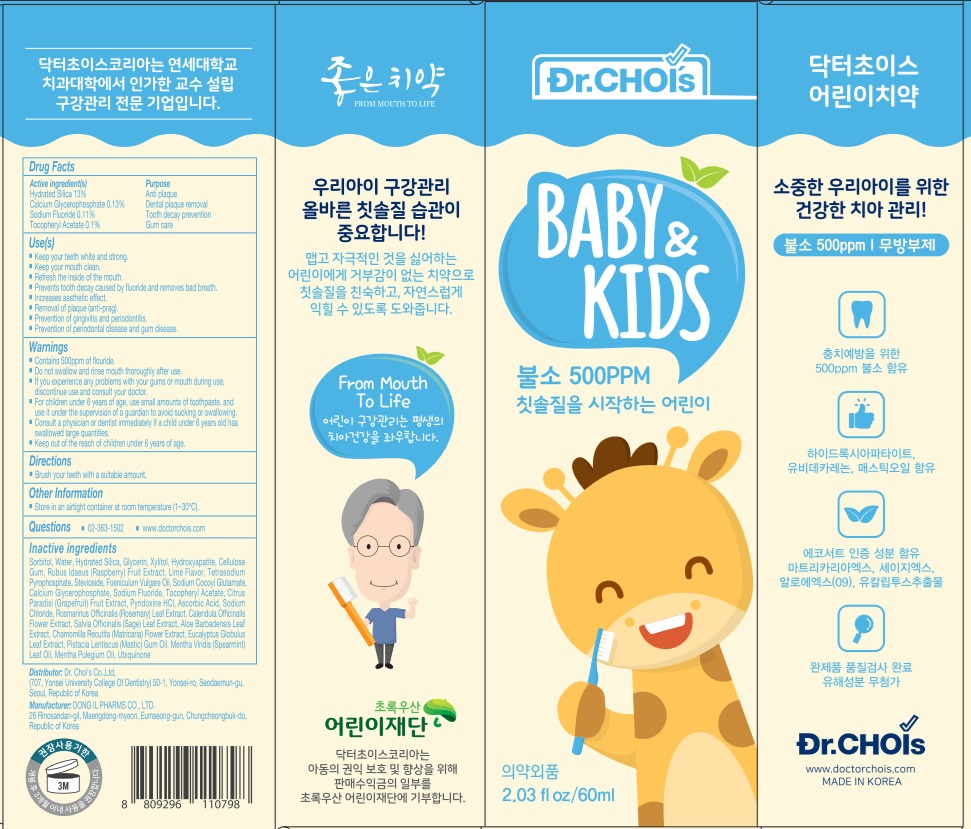 DRUG LABEL: DR.CHOIS TOOTHPASTE STEP TWO KIDS
NDC: 73666-0540 | Form: PASTE, DENTIFRICE
Manufacturer: Doctor Choi`s Korea Co., LTD.
Category: otc | Type: HUMAN OTC DRUG LABEL
Date: 20241114

ACTIVE INGREDIENTS: HYDRATED SILICA 13 g/100 g; CALCIUM GLYCEROPHOSPHATE 0.13 g/100 g; SODIUM FLUORIDE 0.11 g/100 g; .ALPHA.-TOCOPHEROL ACETATE 0.1 g/100 g
INACTIVE INGREDIENTS: SORBITOL; WATER; GLYCERIN

ACTIVE INGREDIENTS

Hydrated Silica 13%
Calcium Glycerophosphate 0.13%
Sodium Fluoride 0.11%
Tocopheryl Acetate 0.1%

PURPOSE

Anti plaque
Dental plaque removal
Tooth decay prevention
Gum care

Uses

■ Keep your teeth white and strong.
■ Keep your mouth clean.
■ Refresh inside of the mouth.
■ Prevents tooth decay caused by fluoride and removes bad breath.
■ Increase aesthetic effect.

■ Removal of plaque (anti-prag)

■ Prevention of gingivitis and periodontitis

■ Prevention of periodontal disease and gum disease.

WARNINGS

■ Contains 500ppm of fluoride.

■ Do not swallow and rinse mouth throughly after use.

■ If you experience any problems with your gums or mouth during use, discontinue use and consult your doctor.

■ For children under 6 year of age, use small amounts of toothpaste, and use it under the supervision of a guardian to avoid sucking or swallowing.

■ Consult a physician or dentist immediately if a child under 6 years old has swallowed large quantities.

■ Keep out of the reach of children under 6 years of age.

KEEP OUT OF REACH OF CHILDREN

■ Keep out of the reach of children under 6 years of age.

Directions

■ Brush your teeth with a suitable amount.

Other Information

■ Store in an airtight container at room temperature (1~30℃).

Questions

■ 02-363-1502
■ www.doctorchois.com

INACTIVE INGREDIENTS

Sorbitol, Water, Glycerin, Xylitol, Hydroxyapatite, Cellulose Gum, Rubus Idaeus (Raspberry) Fruit Extract, Lime Flavor, Tetrasodium Pyrophosphate, Stevioside, Foeniculum Vulgare Oil, Sodium Cocoyl Glutamate, Calcium Glycerophosphate, Sodium Fluoride, Tocopheryl Acetate, Citrus Paradisi (Grapefruit) Fruit Extract, Pyridoxine HCl, Ascorbic Acid, Sodium Chloride, Rosmarinus Officinalis (Rosemary) Leaf Extract, Calendula Officinalis Flower Extract, Salvia Officinalis (Sage) Leaf Extract, Aloe Barbadensis Leaf Extract, "Chamomilla Recutita (Matricaria) Flower Extract", Eucalyptus Globulus Leaf Extract, Pistacia Lentiscus (Mastic) Gum Oil, Mentha Viridis (Spearmint) Leaf Oil, Mentha Pulegium Oil, Ubiquinone